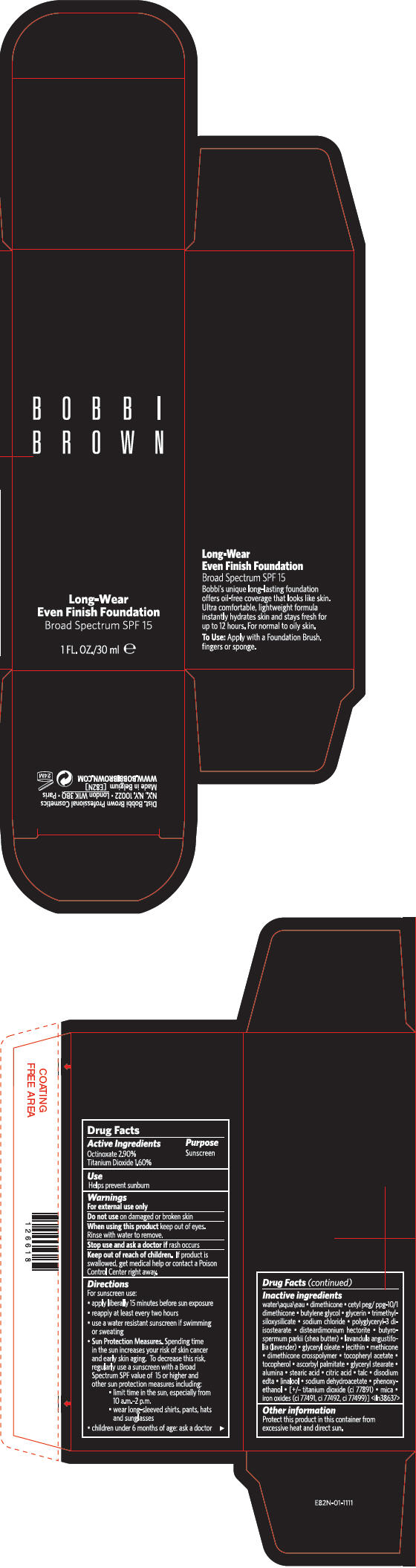 DRUG LABEL: LONG-WEAR EVEN FINISH FOUNDATION BROAD SPECTRUM SPF 15
NDC: 64141-011 | Form: LIQUID
Manufacturer: Bobbi Brown Professional Cosmetics Inc.
Category: otc | Type: HUMAN OTC DRUG LABEL
Date: 20120111

ACTIVE INGREDIENTS: OCTINOXATE 2.9 mL/100 mL; TITANIUM DIOXIDE 1.6 mL/100 mL
INACTIVE INGREDIENTS: water; dimethicone; butylene glycol; glycerin; sodium chloride; shea butter; lavandula angustifolia flower; glyceryl monooleate; alpha-tocopherol acetate; tocopherol; ascorbyl palmitate; glyceryl monostearate; aluminum oxide; stearic acid; citric acid monohydrate; talc; edetate disodium; linalool, (+/-)-; sodium dehydroacetate; phenoxyethanol; mica; ferric oxide red; ferric oxide yellow; ferrosoferric oxide

Long-Wear
Even Finish Foundation
Broad Spectrum SPF 15

Drug Facts

Active Ingredients

Octinoxate 2.90%
Titanium Dioxide 1.60%

Purpose

Sunscreen

Use

Helps prevent sunburn

Warnings

For external use only

Do not use on damaged or broken skin

When using this product keep out of eyes.

Rinse with water to remove.

Stop use and ask a doctor if rash occurs

Keep out of reach of children. If product is swallowed, get medical help or contact a Poison Control Center right away.

Directions

For sunscreen use:

- apply liberally 15 minutes before sun exposure
- reapply at least every two hours
- use a water resistant sunscreen if swimming or sweating
- Sun Protection Measures. Spending time in the sun increases your risk of skin cancer and early skin aging. To decrease this risk, regularly use a sunscreen with a Broad Spectrum SPF value of 15 or higher and other sun protection measures including:
  - limit time in the sun, especially from 10 a.m.-2 p.m.
  - wear long-sleeved shirts, pants, hats and sunglasses
- children under 6 months of age: ask a doctor

Inactive ingredients

water • dimethicone • cetyl peg/ppg-10/1 dimethicone • butylene glycol • glycerin • trimethylsiloxysilicate • sodium chloride • polyglyceryl-3 diisostearate • disteardimonium hectorite • butyrospermum parkii (shea butter) • lavandula angustifolia (lavender) • glyceryl oleate • lecithin • methicone • dimethicone crosspolymer • tocopheryl acetate • tocopherol • ascorbyl palmitate • glyceryl stearate • alumina • stearic acid • citric acid • talc • disodium edta • linalool • sodium dehydroacetate • phenoxyethanol • [+/- titanium dioxide (ci 77891) • mica • iron oxides (ci 77491, ci 77492, ci 77499)]<iln38637>

Other information

Protect this product in this container from excessive heat and direct sun.

Dist. Bobbie Brown Professional Cosmetics
N.Y., N.Y. 10022 • London W1K 3BQ • Paris

PRINCIPAL DISPLAY PANEL - 30 ml Carton

BOBBI
BROWN

Long-Wear
Even Finish Foundation
Broad Spectrum SPF 15

1 FL. OZ./30 ml e